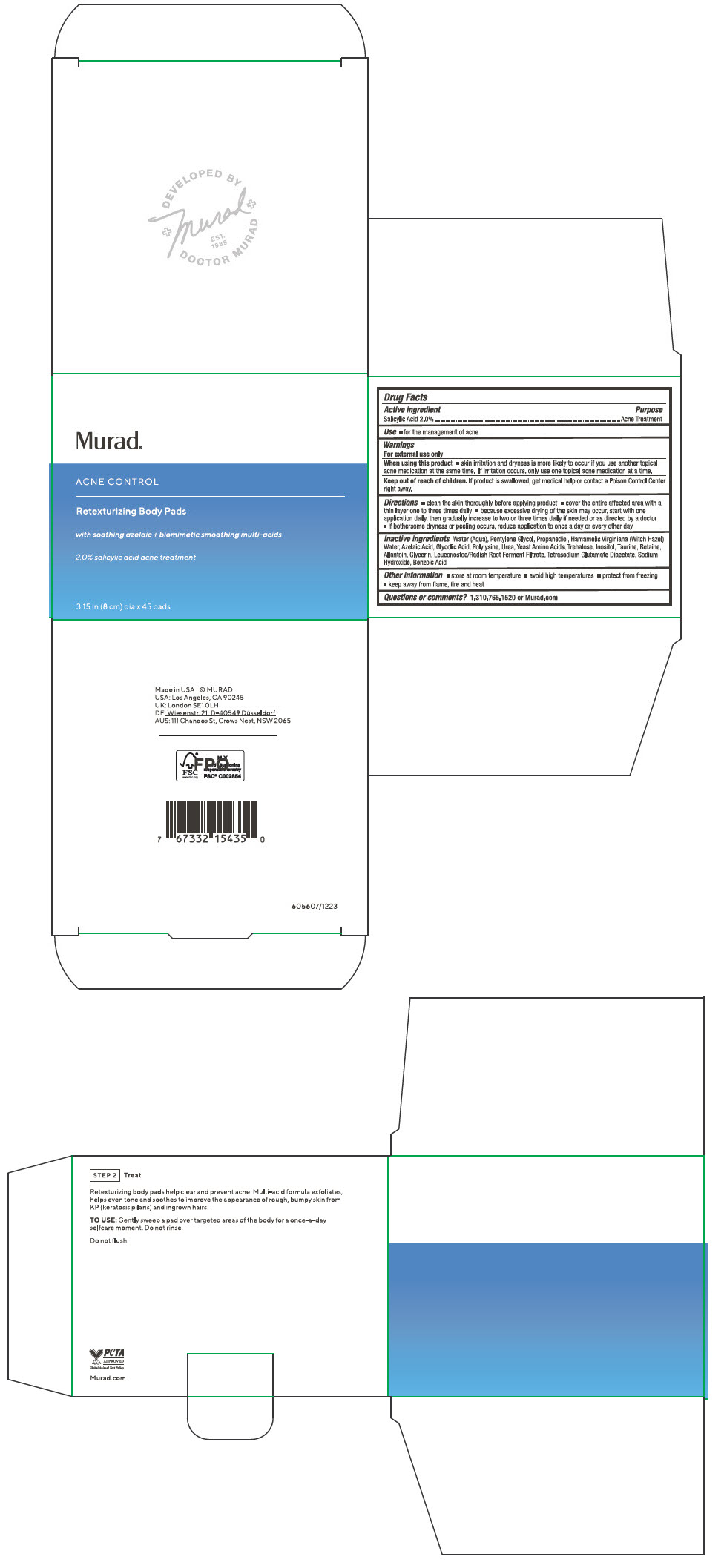 DRUG LABEL: Retexturizing Body Pads
NDC: 70381-126 | Form: SOLUTION
Manufacturer: Murad, LLC
Category: otc | Type: HUMAN OTC DRUG LABEL
Date: 20260116

ACTIVE INGREDIENTS: SALICYLIC ACID 2 g/100 mm
INACTIVE INGREDIENTS: WATER; PENTYLENE GLYCOL; PROPANEDIOL; HAMAMELIS VIRGINIANA TOP WATER; AZELAIC ACID; GLYCOLIC ACID; POLY-L-LYSINE (30000-70000 MW); UREA; AMINO ACIDS, SOURCE UNSPECIFIED; TREHALOSE; INOSITOL; TAURINE; BETAINE; ALLANTOIN; GLYCERIN; LEUCONOSTOC/RADISH ROOT FERMENT FILTRATE; TETRASODIUM GLUTAMATE DIACETATE; SODIUM HYDROXIDE; BENZOIC ACID

Retexturizing Body Pads

Drug Facts

Active ingredients

Salicylic Acid 2.0%

Purpose

Acne Treatment

Use

- for the management of acne

Warnings

For external use only

When using this product

- skin irritation and dryness is more likely to occur if you use another topical acne medication at the same time. If irritation occurs, only use one topical acne medication at a time.

Keep out of reach of children. If product is swallowed, get medical help or contact a Poison Control Center right away.

Directions

- clean the skin thoroughly before applying product
- cover the entire affected area with a thin layer one to three times daily
- because excessive drying of the skin may occur, start with one application daily, then gradually increase to two or three times daily if needed or as directed by a doctor
- if bothersome dryness or peeling occurs, reduce application to once a day or every other day

Inactive ingredients

Water (Aqua), Pentylene Glycol, Propanediol, Hamamelis Virginiana (Witch Hazel) Water, Azelaic Acid, Glycolic Acid, Polylysine, Urea, Yeast Amino Acids, Trehalose, Inositol, Taurine, Betaine, Allantoin, Glycerin, Leuconostoc/Radish Root Ferment Filtrate, Tetrasodium Glutamate Diacetate, Sodium Hydroxide, Benzoic Acid

Other information

- store at room temperature
- avoid high temperatures
- protect from freezing
- keep away from flame, fire and heat

Questions or comments?

1.800.33.MURAD or Murad.com

PRINCIPAL DISPLAY PANEL - 45 Pad Jar Carton

Murad®

ACNE CONTROL

Retexturizing Body Pads

with soothing azelaic + biomimetic smoothing multi-acids

2.0% salicylic acid acne treatment

3.15 in (8 cm) dia x 45 pads